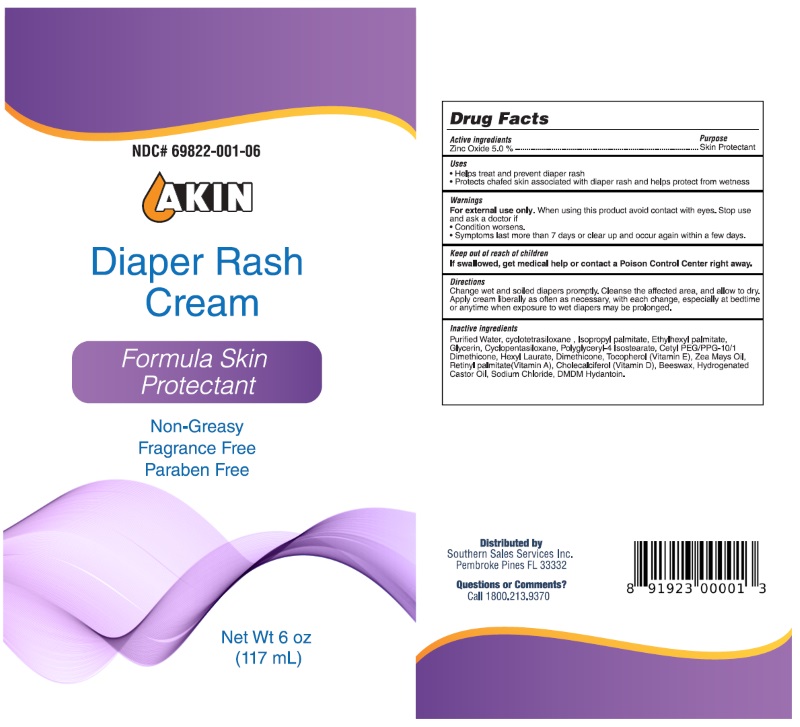 DRUG LABEL: Akin Diaper Rash
NDC: 69822-001 | Form: GEL
Manufacturer: Southern Sales & Service, Inc.
Category: otc | Type: HUMAN OTC DRUG LABEL
Date: 20190425

ACTIVE INGREDIENTS: ZINC OXIDE 5 mg/100 mL
INACTIVE INGREDIENTS: DMDM HYDANTOIN; SODIUM CHLORIDE; HYDROGENATED CASTOR OIL; YELLOW WAX; CHOLECALCIFEROL; VITAMIN A PALMITATE; CORN OIL; DIMETHICONE; TOCOPHEROL; HEXYL LAURATE; CETYL PEG/PPG-10/1 DIMETHICONE (HLB 1.5); POLYGLYCERYL-4 ISOSTEARATE; DIMETHICONE CROSSPOLYMER (450000 MPA.S AT 12% IN CYCLOPENTASILOXANE); GLYCERIN; ETHYLHEXYL PALMITATE; ISOPROPYL PALMITATE; MONOPHENYLHEPTAMETHYLCYCLOTETRASILOXANE; WATER

Active Ingredients

Active Ingredient Purpose

Zinc Oxide 5%...............................................Skin Protectant

INACTIVE INGREDIENT

Purified Water, cyclotetrasiloxane , Isopropyl palmitate, Ethylhexyl palmitate, Glycerin, Cyclopentasiloxane, Polyglyceryl-4 Isostearate, Cetyl PEG/PPG-10/1 Dimethicone, Hexyl Laurate, Dimethicone, Tocopherol (Vitamin E), Zea Mays Oil, Retinyl palmitate(Vitamin A), Cholecalciferol (Vitamin D), Beeswax, Hydrogenated Castor Oil, Sodium Chloride, DMDM Hydantoin.

KEEP OUT OF REACH OF CHILDREN

If swallowed, get medical help or contact a Poison Control Center right away.

INDICATIONS & USAGE

Helps treat and prevent diaper rash.

WARNINGS

For external use only. When using this product avoid contact with eyes. Stop use and ask a doctor if
• Condition worsens.
• Symptoms last more than 7 days or clear up and occur again within a few days.

DOSAGE & ADMINISTRATION

Change wet and soiled diapers promptly. Cleanse the affected area, and allow to dry. Apply cream liberally as often as necessary, with each change, especially at bedtime or anytime when exposure to wet diapers may be prolonged.

PURPOSE

• Helps treat and prevent diaper rash.
• Protects chafed skin associated with diaper rash and helps protect from wetness.